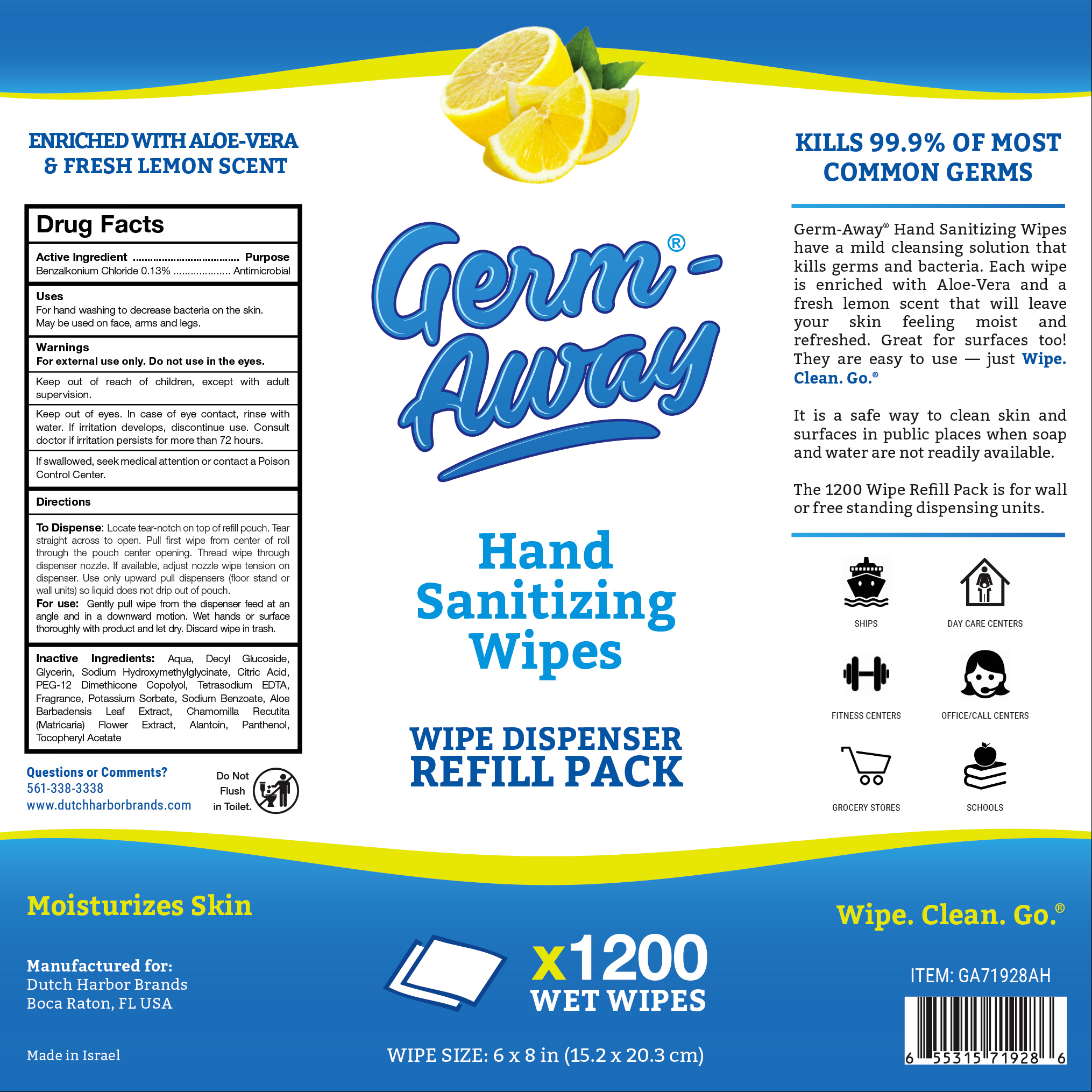 DRUG LABEL: Germ-Away
NDC: 74680-102 | Form: CLOTH
Manufacturer: Unico International Trading Corp
Category: otc | Type: HUMAN OTC DRUG LABEL
Date: 20260108

ACTIVE INGREDIENTS: BENZALKONIUM CHLORIDE 1.3 mg/1 g
INACTIVE INGREDIENTS: 3,7-DIMETHYL-1-OCTANOL; DIPHENYL ETHER; COUMARIN; EUCALYPTOL; POTASSIUM SORBATE; PANTHENOL; TETRAHYDROLINALOOL; 2,2'-OXYDIPROPANOL; ANHYDROUS CITRIC ACID; WATER; .ALPHA.-TOCOPHEROL ACETATE; CHAMOMILE; ALOE VERA LEAF; 2-ISOBUTYL-4-METHYLTETRAHYDROPYRAN-4-OL; PEG-12 DIMETHICONE (300 CST); SODIUM HYDROXYMETHYLGLYCINATE; DECYL GLUCOSIDE; SODIUM BENZOATE; EDETATE SODIUM; GLYCERIN; ALLANTOIN

Germ-Away

Active ingredient

Benzalkonium chloride 0.1%

Purpose

Anti-bacterial

Keep our of the reach of children

Keep out of reach of children, except with adult supervision.

Warnings

For external use only. Do not use in the eyes.

Keep out of eyes. In case of eye contact, rinse with water. If irritation develops, discontinue use. Consult doctor if irritation persists for more than 72 hours.

If swallowed, seek medical attention or contact a Poison Control Center.

Directions

Pull one sheet from pack. Sanitize hands or other affected area. Discard in trash after use. Do not flush.

Fragrance

Aqua, Decyl Glucoside, Glycerin, Sodium Hydroxymethylglycinate, Citric Acid, PEG-12 Dimethicone Copolyol, Tetrasodium EDTA, Potassium Sorbate, Sodium Benzoate, Aloe Barbadensis Leaf Extract, Chamomilla Recutita (Matricaria) Flower Extract, Allantoin, Panthenol, Tocopheryl Acetate, Fragranc

Directions

Locate tear-notch on top of refill pouch. Tear straight across to open. Pull first wipe from center of roll through the pouch center opening. Thread wipe through dispenser nozzle. Use only upward pull dispensers (floor stand or wall units) so liquid does not drip out of pouch.